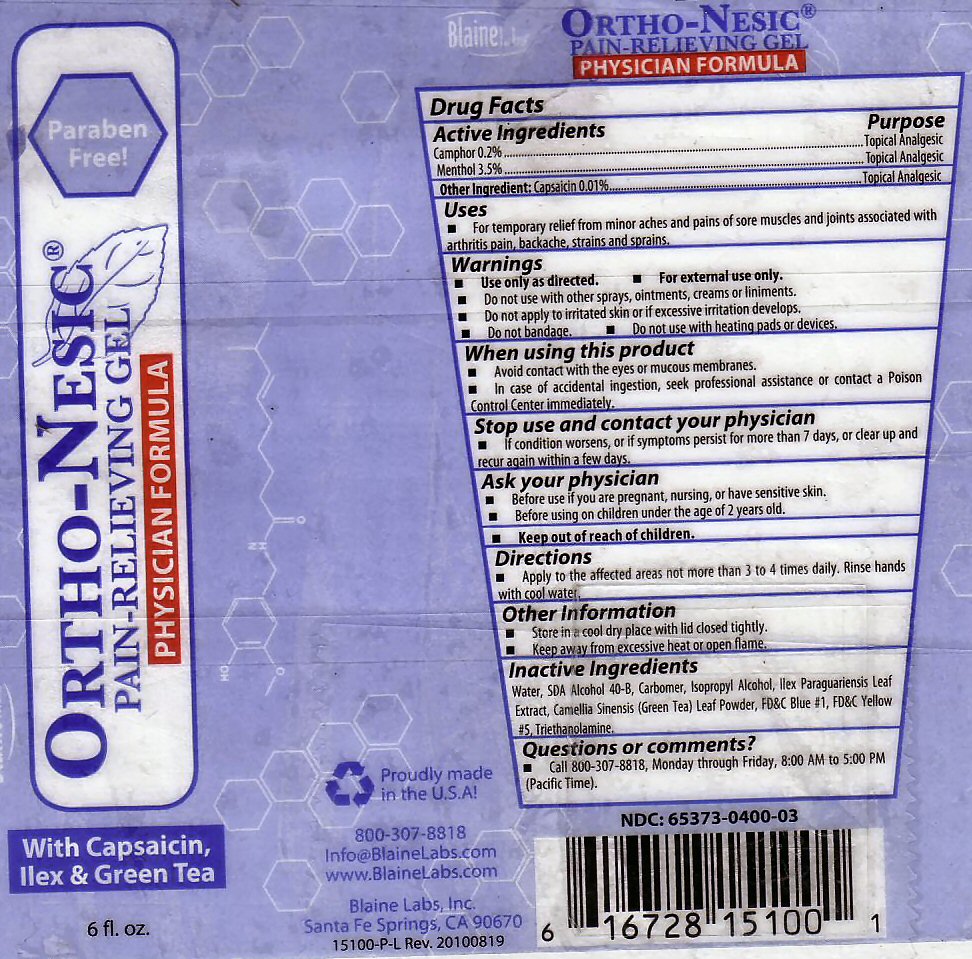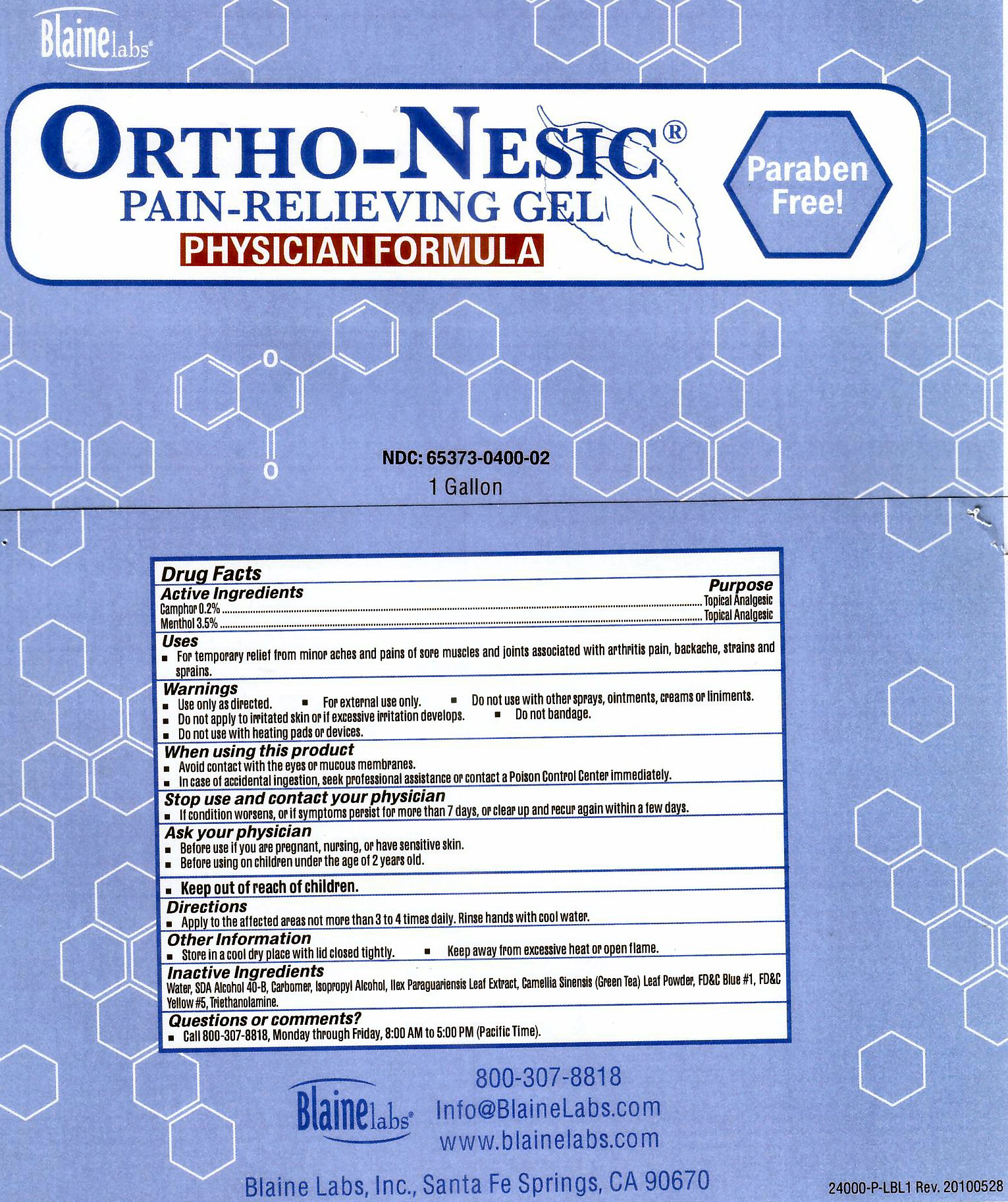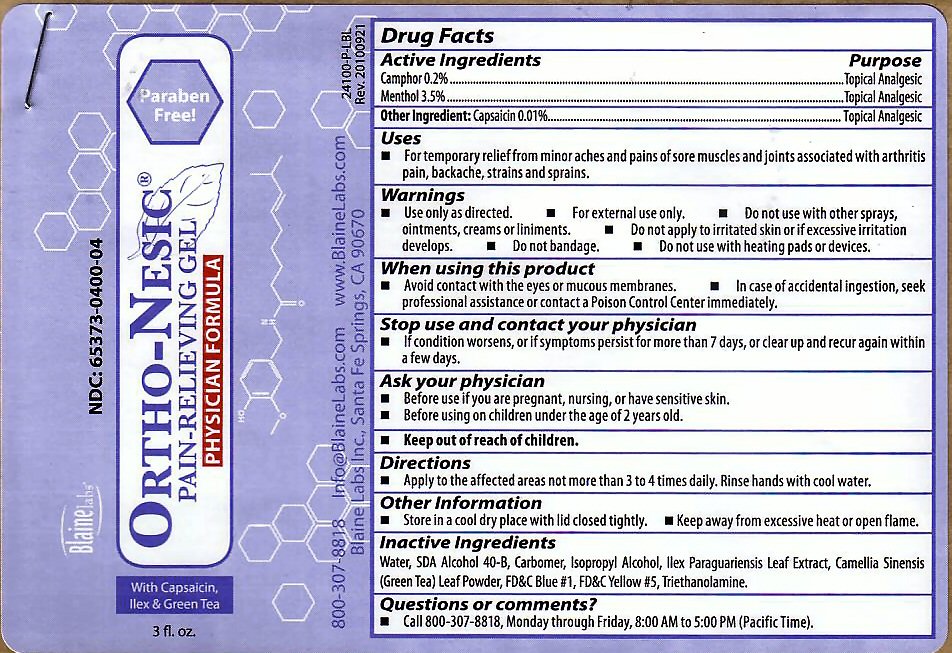 DRUG LABEL: Ortho-Nesic With Capsaicin
NDC: 65373-401 | Form: GEL
Manufacturer: Blaine Labs Inc.
Category: otc | Type: HUMAN OTC DRUG LABEL
Date: 20110125

ACTIVE INGREDIENTS: MENTHOL 3.5 g/100 g; CAMPHOR (SYNTHETIC) 0.2 g/100 g
INACTIVE INGREDIENTS: WATER; ALCOHOL; CARBOMER 934; ISOPROPYL ALCOHOL; ILEX PARAGUARIENSIS LEAF; GREEN TEA LEAF ; FD&C BLUE NO. 1; FD&C YELLOW NO. 5; TROLAMINE; CAPSAICIN

Active Ingredients

Camphor - 0.2%

Menthol - 3/5%

Inactive Ingredients

Water, SDA Alcohol 40-B, Carbomer, Isopropyl Alcohol, Ilex Paraguariensis Leaf Extract, Camelia Sinensis (Green Tea) Leaf Powder, FD and C Blue #1, FD and C Yellow #5, Triethanolamine

Purpose

Topical Analgesic

Uses

For temporary relief from minor aches and pains of sore muscles and joints associated with arthritis pain, backache, strains and sprains

Directions: Apply to the affected areas not more than 3 to 4 times daily. Rinse hands with cool water.

Ask Your Physician

Before use if you are pregnant, nursing or have sensitive skin

Before use on children under the age of 2 years old

Keep Out Of The Reach Of Children

Stop Use and Contact Your Physician if conditions worsen or if symptoms persist for more than 7 days, or clear up and recur again within a few days.

When Using This Product

Avoid contact with the eyes or mucous membranes. In case of accidental ingestion, seek professional assistance or contact a poison control center immediately.

Other Information

Store in a cool dry place with lid closed tightly. Keep away from excessive heat or open flame

Warnings

Use only as directed. For external use only. Do not use with other sprays or ointments creams or liniments. Do not apply to irritated skin or if excessive irritation develops. Do Not bandage. Do not sue with heating pads or devices.

Ortho-Nesic Label

Ortho-Nesic Pain Relieving Gel Penetrates Fast and Deep Relieves Sore Muscles and Joints

Physician Formula Greaseless, Stainless Great for Arthritis and Sports Injuries Stops the Pain. With Capsaicin, Ilex and Green Tea. Paraben Free